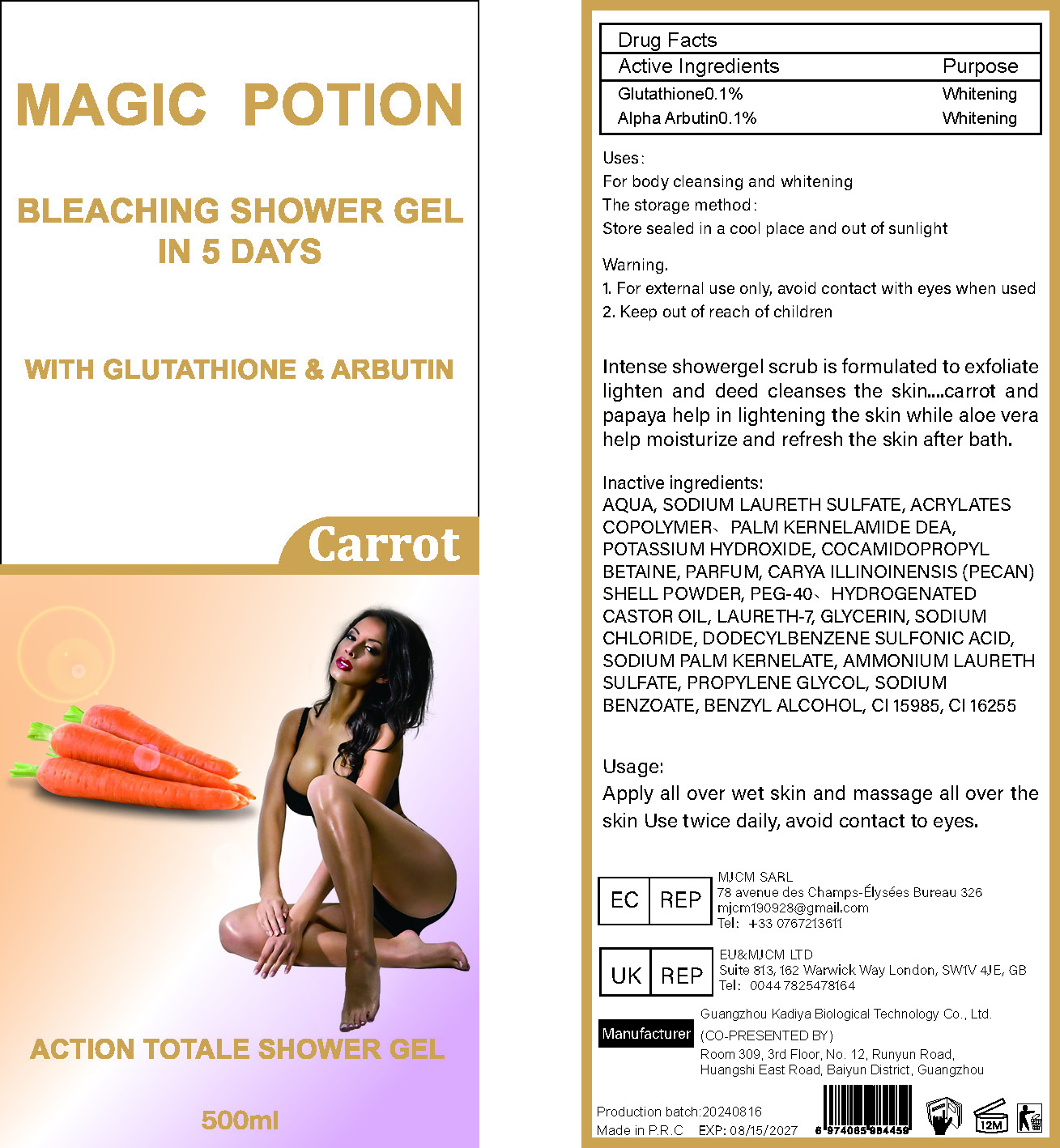 DRUG LABEL: MAGIC POTION BLEACHING SHOWER GELIN
NDC: 84423-033 | Form: EMULSION
Manufacturer: Guangzhou Kadiya Biotechnology Co., Ltd.
Category: otc | Type: HUMAN OTC DRUG LABEL
Date: 20240825

ACTIVE INGREDIENTS: GLUTATHIONE 0.5 mg/500 mL; ALPHA-ARBUTIN 0.5 mg/500 mL
INACTIVE INGREDIENTS: AMMONIUM LAURETH-12 SULFATE; FD&C YELLOW NO. 6; SODIUM PALM KERNELATE; PONCEAU 4R; WATER; SODIUM LAURETH SULFATE; SODIUM CHLORIDE; COCAMIDOPROPYL BETAINE; LAURETH-7; POTASSIUM HYDROXIDE; HYDROGENATED CASTOR OIL; BENZYL ALCOHOL; CARYA ILLINOINENSIS POLLEN; POLYETHYLENE GLYCOL 2000; SODIUM BENZOATE; DODECYLBENZENESULFONIC ACID; GLYCERIN

PURPOSE

For body cleansing and whitening

INACTIVE INGREDIENT

AQUA、SODIUM LAURETH SULFATE、ACRYLATES COPOLYMER、PALM KERNELAMIDE DEA、POTASSIUM HYDROXIDE、COCAMIDOPROPYL BETAINE、PARFUM、CARYA ILLINOINENSIS (PECAN) SHELL POWDER、PEG-40、HYDROGENATED CASTOR OIL、LAURETH-7、GLYCERIN、SODIUM CHLORIDE、DODECYLBENZENE SULFONIC ACID
、SODIUM PALM KERNELATE、AMMONIUM LAURETH SULFATE、PROPYLENE GLYCOL、SODIUM BENZOATE、BENZYL ALCOHOL、CI 15985、CI 16255

WARNINGS

1、For external use only, avoid contact with eyes when used
2、Keep out of reach of children

INDICATIONS AND USAGE

Intense showergel scrub is formulated to exfoliate lighten and deed cleanses the skin.... carrot and papaya help in lightening the skin while aloe veral help moisturize and refresh the skin after bath.

DOSAGE AND ADMINISTRATION

Apply all over wet skin and massage all over the skin Use twice daily, avoid contact to eyes.

KEEP OUT OF REACH OF CHILDREN SECTION

Active Ingredients
Glutathione0.1%
Alpha Arbutin0.1%

PACKAGE LABEL

Active Ingredients
Glutathione0.1%
Alpha Arbutin0.1%

Uses：
For body cleansing and whitening
The storage method：
Store sealed in a cool place and out of sunlight

Warning.
1、For external use only, avoid contact with eyes when used
2、Keep out of reach of children

Inactive ingredients：
AQUA、SODIUM LAURETH SULFATE、ACRYLATES COPOLYMER、PALM KERNELAMIDE DEA、POTASSIUM HYDROXIDE、COCAMIDOPROPYL BETAINE、PARFUM、CARYA ILLINOINENSIS (PECAN) SHELL POWDER、PEG-40、HYDROGENATED CASTOR OIL、LAURETH-7、GLYCERIN、SODIUM CHLORIDE、DODECYLBENZENE SULFONIC ACID
、SODIUM PALM KERNELATE、AMMONIUM LAURETH SULFATE、PROPYLENE GLYCOL、SODIUM BENZOATE、BENZYL ALCOHOL、CI 15985、CI 16255